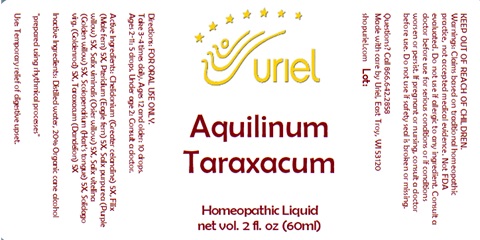 DRUG LABEL: Aquilinum Taraxacum
NDC: 48951-1069 | Form: LIQUID
Manufacturer: Uriel Pharmacy Inc.
Category: homeopathic | Type: HUMAN OTC DRUG LABEL
Date: 20240326

ACTIVE INGREDIENTS: CHELIDONIUM MAJUS 5 [hp_X]/1 mL; DRYOPTERIS FILIX-MAS ROOT 5 [hp_X]/1 mL; PTERIDIUM AQUILINUM WHOLE 5 [hp_X]/1 mL; SALIX PURPUREA BARK 5 [hp_X]/1 mL; WILLOW BARK 5 [hp_X]/1 mL; SALIX ALBA FLOWER 5 [hp_X]/1 mL; ASPLENIUM SCOLOPENDRIUM TOP 5 [hp_X]/1 mL; SOLIDAGO VIRGAUREA FLOWERING TOP 5 [hp_X]/1 mL; TARAXACUM PALUSTRE ROOT 5 [hp_X]/1 mL
INACTIVE INGREDIENTS: WATER; ALCOHOL

Aquilinum Taraxacum

INDICATIONS AND USAGE

Directions: FOR ORAL USE ONLY.

DOSAGE AND ADMINISTRATION

Take 3-4 times daily. Ages 12 and older: 10 drops. Ages 2-11: 5 drops. Under age 2: Consult a doctor.

ACTIVE INGREDIENT

Active Ingredients: Chelidonium (Greater celandine) 5X, Filix (Male fern) 5X, Pteridium (Eagle fern)5X, Salix purpurea (Purple willow) 5X, Salix viminalis (Osier willow) 5X, Salix vitellina (Golden willow) 5X, Scolopendrium (Hart’s tongue) 5X, Solidago virg. (Goldenrod) 5X, Taraxacum (Dandelion) 5X

Inactive Ingredients: Distilled water, 20% Organic cane alcohol

prepared using rhythmical processes

PURPOSE

Use: Temporary relief of digestive upset.

KEEP OUT OF REACH OF CHILDREN.

WARNINGS

Warnings: Claims based on traditional homeopathic practice, not accepted medical evidence. Not FDA evaluated. Do not use if allergic to any ingredient. Consult a doctor before use for serious conditions or if conditions worsen or persist. If pregnant or nursing, consult a doctor before use. Do not use if safety seal is broken or missing.

QUESTIONS

Questions? Call 866.642.2858 Made with care by Uriel, East Troy, WI 53120 shopuriel.com Lot: